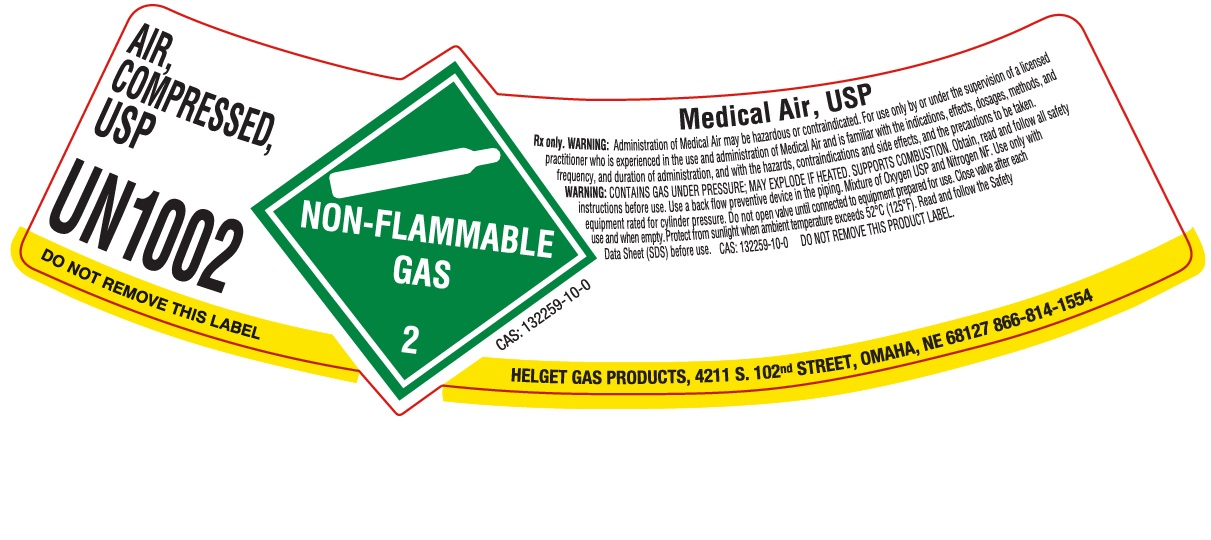 DRUG LABEL: Reconstituted Air
NDC: 52086-020 | Form: GAS
Manufacturer: Helget Gas Products
Category: prescription | Type: HUMAN PRESCRIPTION DRUG LABEL
Date: 20251205

ACTIVE INGREDIENTS: OXYGEN 230.5 mL/1 L

Reconstituted Air

PACKAGE LABEL

AIR, COMPRESSED USP

UN1002

DO NOT REMOVE THIS LABEL

Medical Air, USP

Rx only. WARNING: Administration of Medical Air may be hazardous or contraindicated. For use only by or under the supervision of a licensed practitioner who is experienced in the use and administration of Medical Air and is familiar with the indications, effects, dosages, methods, and frequency, and duration of administration, and with the hazards, contraindications and side effects, and the precautions to be taken. WARNING: CONTAINS GAS UNDER PRESSURE; MAY EXPLODE IF HEATED. SUPPORTS COMBUSTION. Obtain, read and follow all safety instructions before use. Use a back flow preventive device in the piping. Mixture of Oxygen USP and Nitrogen NF. Use only with equipment rated for cylinder pressure. Do not open valve until connected to equipment prepared for use. Close valve after each use and when empty. Protect from sunlight when ambient temperature exceeds 52 C (125 F). Read and follow the Safety Data Sheet (SDS) before use. CAS: 132259-10-0 DO NOT REMOVE THIS PRODUCT LABEL.

HELGET GAS PRODUCTS, 4211 S. 102ND STREET, OMAHA, NE 68127 866-814-1554